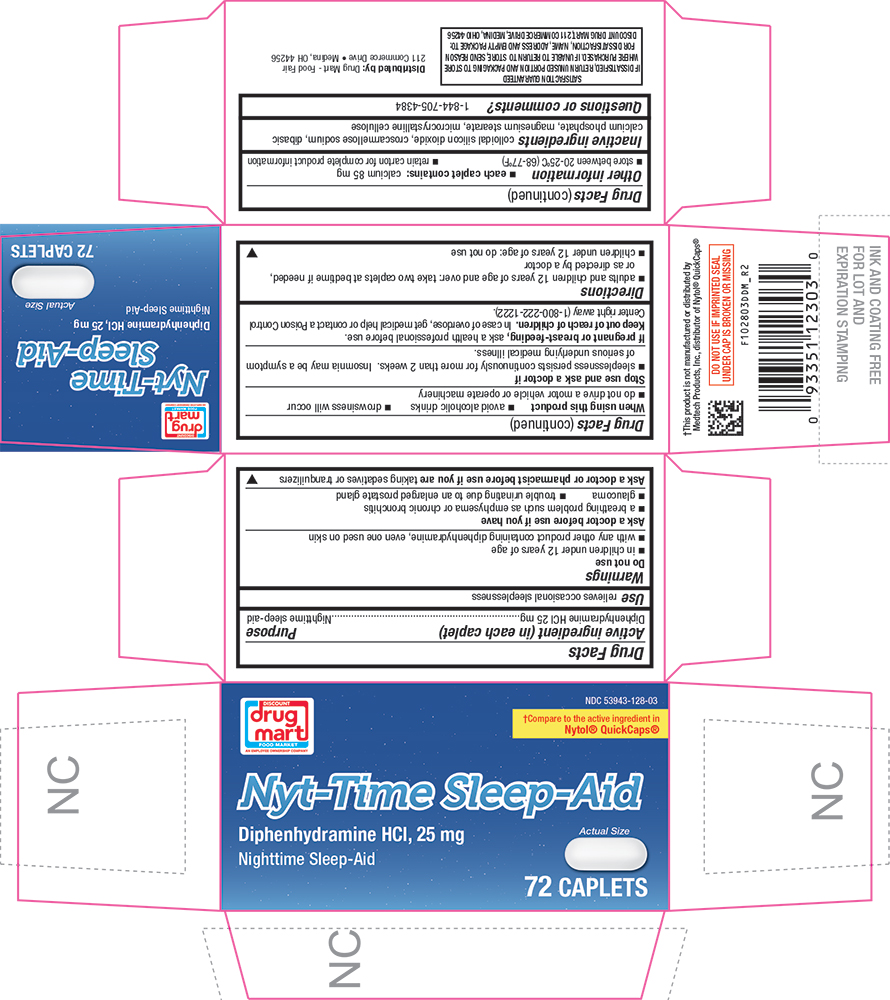 DRUG LABEL: Nyt Time Sleep Caps
NDC: 53943-128 | Form: TABLET
Manufacturer: DISCOUNT DRUG MART
Category: otc | Type: HUMAN OTC DRUG LABEL
Date: 20251023

ACTIVE INGREDIENTS: DIPHENHYDRAMINE HYDROCHLORIDE 25 mg/1 1
INACTIVE INGREDIENTS: SILICON DIOXIDE; CROSCARMELLOSE SODIUM; CALCIUM PHOSPHATE, DIBASIC, ANHYDROUS; MAGNESIUM STEARATE; CELLULOSE, MICROCRYSTALLINE

1028-DDM-2025-0630

Drug Facts

Active ingredient (in each caplet)

Diphenhydramine HCl 25 mg

Purpose

Nighttime sleep-aid

Use

relieves occasional sleeplessness

Warnings

Do not use

- in children under 12 years of age
- with any other product containing diphenhydramine, even one used on skin

Ask a doctor before use if you have

- glaucoma
- a breathing problem such as emphysema or chronic bronchitis
- trouble urinating due to an enlarged prostate gland

Ask a doctor or pharmacist before use if you aretaking sedatives or tranquilizers

When using this productavoid alcoholic drinks

Stop use and ask a doctor ifsleeplessness persists continuously for more than 2 weeks. Insomnia may be a symptom of serious underlying medical illness.

PREGNANCY OR BREAST FEEDING

If pregnant or breast-feeding,ask a health professional before use.

Keep out of reach of children.In case of overdose, get medical help or contact a Poison Control Center right away.

Directions

- adults and children 12 years of age and over: take two caplets (50 mg) at bedtime if needed, or as directed by a doctor

Other information

- each caplet contains: calcium 85 mg
- store at room temperature 15°-30°C (59°-86°F)
- retain carton for complete product information

Inactive ingredients

colloidal silicon dioxide, croscarmellose sodium, dibasic calcium phosphate, magnesium stearate, microcrystalline cellulose

PRINCIPAL DISPLAY PANEL

DISCOUNT drug mart FOOD FAIR

NDC 53943-138-03

†Compare to the active ingredient in Nytol® QuickCaps®

Nyt-Time Sleep-Aid

Diphenhydramine HCl, 25 mg

Nighttime Sleep-Aid

Actual Size

72 Caplets